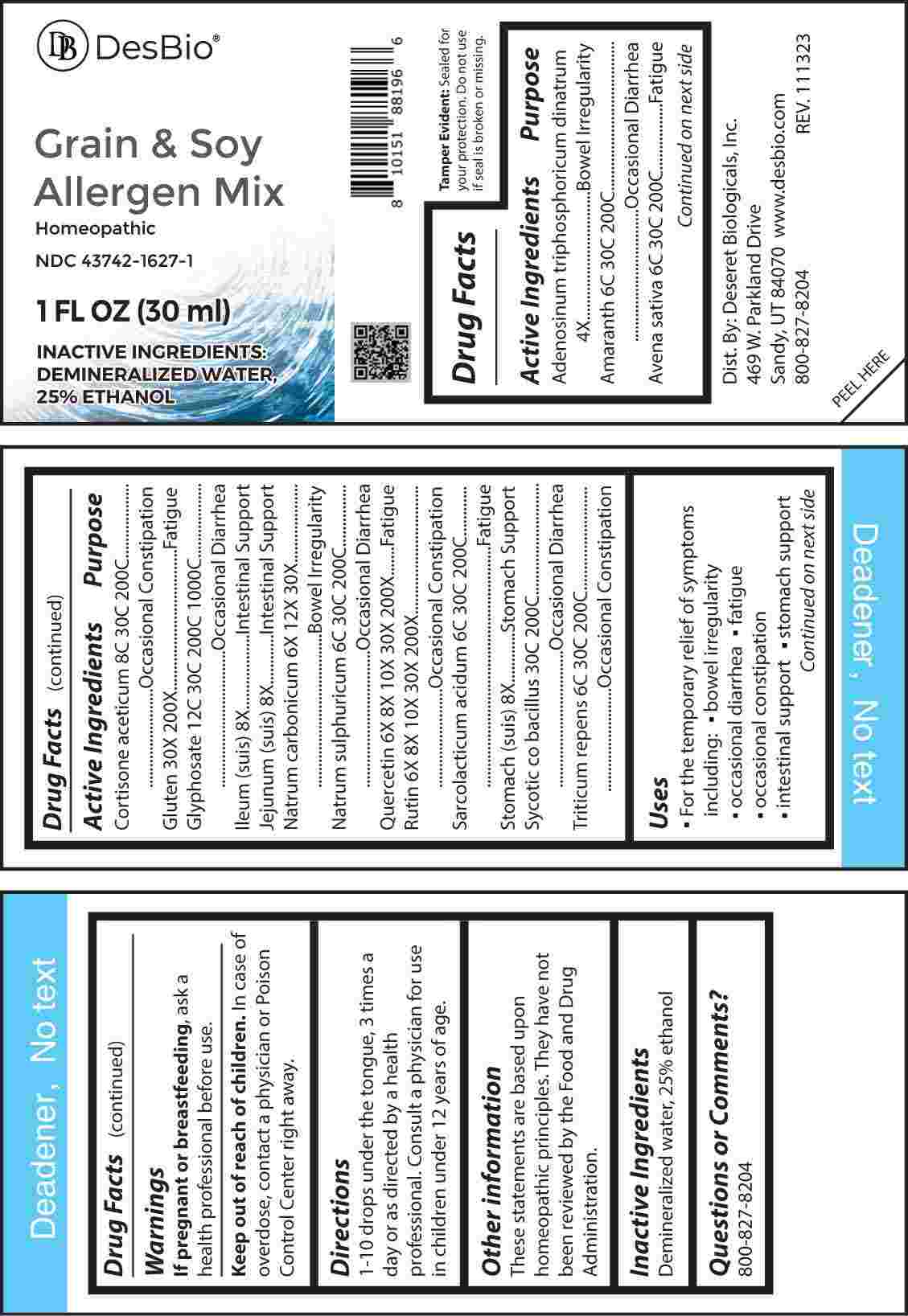 DRUG LABEL: Grain and Soy Allergen Mix
NDC: 43742-1627 | Form: LIQUID
Manufacturer: Deseret Biologicals, Inc.
Category: homeopathic | Type: HUMAN OTC DRUG LABEL
Date: 20240222

ACTIVE INGREDIENTS: ADENOSINE TRIPHOSPHATE DISODIUM 4 [hp_X]/1 mL; QUERCETIN 6 [hp_X]/1 mL; RUTIN 6 [hp_X]/1 mL; SODIUM CARBONATE 6 [hp_X]/1 mL; SUS SCROFA ILEUM 8 [hp_X]/1 mL; SUS SCROFA JEJUNUM 8 [hp_X]/1 mL; SUS SCROFA STOMACH 8 [hp_X]/1 mL; WHEAT GLUTEN 30 [hp_X]/1 mL; AMARANTH 6 [hp_C]/1 mL; AVENA SATIVA FLOWERING TOP 6 [hp_C]/1 mL; SODIUM SULFATE 6 [hp_C]/1 mL; LACTIC ACID, L- 6 [hp_C]/1 mL; ELYMUS REPENS ROOT 6 [hp_C]/1 mL; CORTISONE ACETATE 8 [hp_C]/1 mL; GLYPHOSATE 12 [hp_C]/1 mL; ENTEROCOCCUS FAECALIS 30 [hp_C]/1 mL
INACTIVE INGREDIENTS: WATER; ALCOHOL

DRUG FACTS:

ACTIVE INGREDIENTS:

Adenosinum Triphosphoricum Dinatrum 4X, Amaranth 6C, 30C, 200C, Avena Sativa 6C, 30C, 200C, Cortisone Aceticum 8C, 30C, 200C, Gluten 30X, 200X, Glyphosate 12C, 30C, 200C, 1000C, Ileum (Suis) 8X, Jejunum (Suis) 8X, Natrum Carbonicum 6X, 12X, 30X, Natrum Sulphuricum 6C, 30C, 200C, Quercetin 6X, 8X, 10X, 30X, 200X, Rutin 6X, 8X, 10X, 30X, 200X, Sarcolacticum Acidum 6C, 30C, 200C, Stomach (Suis) 8X, Sycotic Co Bacillus 30C, 200C, Triticum Repens 6C, 30C, 200C.

PURPOSE:

Adenosinum Triphosphoricum Dinatrum – Bowel Irregularity, Amaranth – Occasional Diarrhea, Avena Sativa - Fatigue, Cortisone Aceticum – Occasional Constipation, Gluten - Fatigue, Glyphosate – Occasional Diarrhea, Ileum (Suis) – Intestinal Support, Jejunum (Suis) – Intestinal Support, Natrum Carbonicum – Bowel Irregularity, Natrum Sulphuricum – Occasional Diarrhea, Quercetin - Fatigue, Rutin – Occasional Constipation, Sarcolacticum Acidum - Fatigue, Stomach (Suis) – Stomach Support, Sycotic Co Bacillus – Occasional Diarrhea, Triticum Repens – Occasional Constipation

USES:

• For the temporary relief of symptoms including:

• bowel irregularity • occasional diarrhea • fatigue • occasional constipation intestinal support • stomach support

These statements are based upon homeopathic principles. They have not been reviewed by the Food and Drug Administration.

WARNINGS:

If pregnant or breast-feeding, ask a health professional before use.

Keep out of reach of children. In case of overdose, contact a physician or Poison Control Center right away.

Tamper Evident: Sealed for your protection. Do not use if seal is broken or missing.

KEEP OUT OF REACH OF CHILDREN:

In case of overdose, contact a physician or Poison Control Center right away.

DIRECTIONS:

1-10 drops under the tongue, 3 times a day or as directed by a health professional. Consult a physician for use in children under 12 years of age.

INACTIVE INDICATIONS:

Demineralized water, 25% ethanol

QUESTIONS:

Dist. By: Deseret Biologicals, Inc.
469 W. Parkland Drive
Sandy, UT 84070

www.desbio.com

800-827-8204

PACKAGE LABEL DISPLAY:

DesBio

Grain & Soy

Allergen Mix

Homeopathic

NDC 43742-1627-1

1 FL OZ (30 ml)